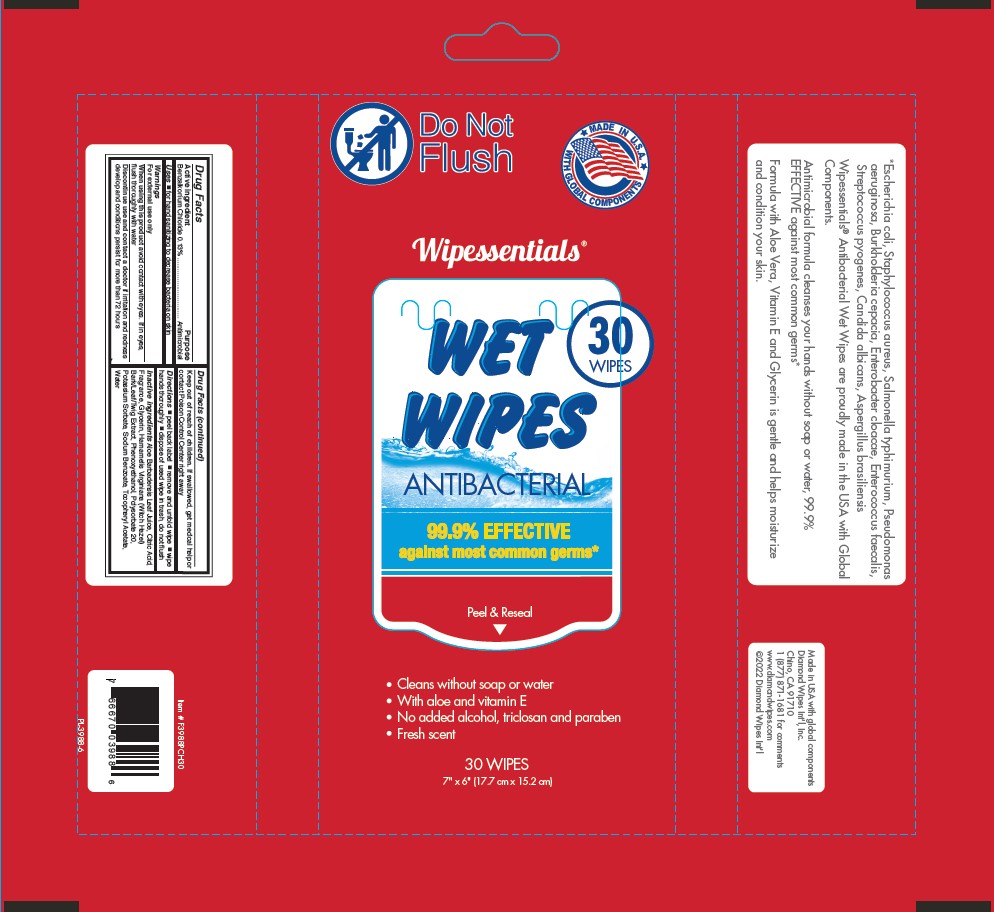 DRUG LABEL: Benzalkonium Chloride
NDC: 64709-100 | Form: SWAB
Manufacturer: Diamond Wipes International
Category: otc | Type: HUMAN OTC DRUG LABEL
Date: 20250911

ACTIVE INGREDIENTS: BENZALKONIUM CHLORIDE 0.13 mg/1 mL
INACTIVE INGREDIENTS: WATER; SODIUM BENZOATE; GLYCERIN; CITRIC ACID MONOHYDRATE; HAMAMELIS VIRGINIANA TOP; PHENOXYETHANOL; ALOE VERA LEAF; POTASSIUM SORBATE; .ALPHA.-TOCOPHEROL ACETATE; POLYSORBATE 20

Wipessentials®

Active ingredient

Benzalkonium Chloride 0.13%

Purpose

Antimicrobial

Uses

■ for hand sanitizing to decrease bacteria on skin

Warnings

For external use only

When using this product avoid contact with eyes. If in eyes, flush thoroughly with water

Discontinue use and contact a doctor if irritation and redness develop and conditions persist for more than 72 hours

Keep out of reach of children. If swallowed, get medical help or contact Poison Control Center right away

Directions

■peel back label ■remove and unfold wipe ■wipe hands thoroughly ■dispose of used wipe in trash, do not flush

Inactive ingredients

Aloe Barbadensis Leaf Juice, Citric Acid, Fragrance, Glycerin, Hamamelis Virginiana (Witch Hazel) Bark/Leaf/Twig Extract, Phenoxyethanol, Polysorbate 20, Potassium Sorbate, Sodium Benzoate, Tocopheryl Acetate, Water

Label

Do Not Flush

MADE IN U.S.A. WITH GLOBAL COMPONENTS

Wipessentials®

WET WIPES30 WIPES

ANTIBACTERIAL

99.9% EFFECTIVE against most common germs*

Peel & Reseal

• Cleans without soap or water
• With aloe and vitamin E
• No added alcohol, triclosan and paraben
• Fresh scent

30 WIPES7" x 6" (17.7 cm x 15.2 cm)

*Escherichia coli, Staphylococcus aureus, Salmonella typhimurium, Pseudomonas aeruginosa, Burkholderia cepacia, Enterobacter cloacae, Enterococcus faecalis, Streptococcus pyogenes, Candida albicans, Aspergillus brasiliensis

Wipessentials® Antibacterial Wet Wipes are proudly made in the USA with Global Components.

Antimicrobial formula cleanses your hands without soap or water, 99.9% EFFECTIVE against most common germs*
Formula with Aloe Vera, Vitamin E and Glycerin is gentle and helps moisturize and condition your skin.

Made in USA with global components
Diamond Wipes Int'l, Inc.
Chino, CA 91710
1 (877) 871-1681 for comments
www.diamondwipes.com
©2022 Diamond Wipes Int'l

Drug Facts
Active ingredient Purpose
Benzalkonium Chloride 0.13% ............. Antimicrobial

Uses ■for hand sanitizing to decrease bacteria on skin

Warnings
For external use only
When using this product avoid contact with eyes. If in eyes, flush thoroughly with water
Discontinue use and contact a doctor if irritation and redness develop and conditions persist for more than 72 hours
Keep out of reach of children. If swallowed, get medical help or contact Poison Control Center right away

Directions ■peel back label ■remove and unfold wipe ■wipe hands thoroughly ■dispose of used wipe in trash, do not flush

Inactive ingredients Aloe Barbadensis Leaf Juice, Citric Acid, Fragrance, Glycerin, Hamamelis Virginiana (Witch Hazel)
Bark/Leaf/Twig Extract, Phenoxyethanol, Polysorbate 20, Potassium Sorbate, Sodium Benzoate, Tocopheryl Acetate, Water

Item # F3988PCH30

7 66670 03988 6

PL-3988-6